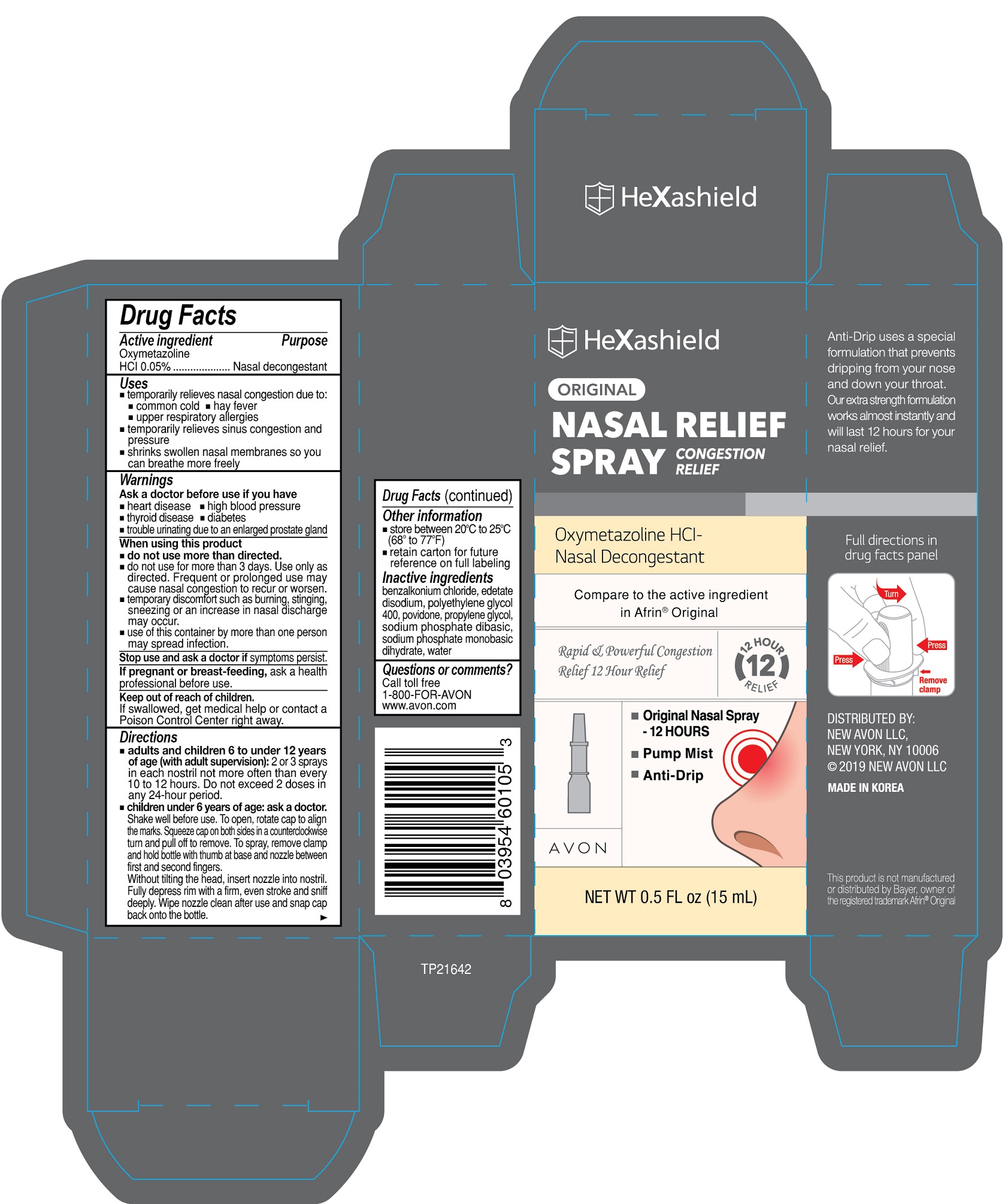 DRUG LABEL: AVON HeXashield Congestion Relief
NDC: 43136-105 | Form: SPRAY
Manufacturer: Tai Guk Pharm. Co., Ltd.
Category: otc | Type: HUMAN OTC DRUG LABEL
Date: 20250101

ACTIVE INGREDIENTS: OXYMETAZOLINE HYDROCHLORIDE 0.05 g/1 mL
INACTIVE INGREDIENTS: WATER; POVIDONE; SODIUM PHOSPHATE, DIBASIC; SODIUM PHOSPHATE, MONOBASIC, DIHYDRATE; POLYETHYLENE GLYCOL 400; PROPYLENE GLYCOL; EDETATE DISODIUM

AVON HeXashield Nasal Relief Spray Congestion Relief Original

Active Ingredient

Oxymetazoline HCl 0.05%

Purpose

Nasal decongestant

Uses

- temporarily relieves nasal congestion due to:

- common cold - hay fever

- upper respiratory allergies

- temporarily relieves sinus congestion and pressure
- shrinks swollen nasal membranes so you can breathe more freely

Warnings

For external use only.

Ask a doctor before use if you have

- heart disease
- high blood pressure
- diabetes
- thyroid disease
- trouble urinating due to an enlarged prostate gland

When using this product

- do not use more than directed
- do not use for more than 3 days. Use only as directed. Frequent or prolonged use may cause nasal congestion to recur or worsen.
- temporary discomfort such as burning, stinging, sneezing or an increase in nasal discharge may occur.
- use of this container by more than one person may spread infection.

Stop use and ask a doctor if :

- symptoms persist.

If pregnant or breast-feeding,

ask a health professional before use.

Keep out of reach of children.

If swallowed, get medical help or contact a Poison Control Center right away.

Directions

- adults and children 6 to under 12 years of age (with adult supervision):2 or 3 sprays in each nostril not more often than every 10 to 12 hours. Do not exceed 2 doses in any 24-hour period.
- children under 6 years of age: ask a doctor:Shake well before use. To open, rotate cap to align the marks. Squeeze cap on both sides in a counterclockwise turn and pull off to remove. To spray, remove clamp and hold bottle with thumb at base and nozzle between first and second fingers. Without tilting the head, insert nozzle into nostril. Fully depress rim with a firm, even stroke and sniff deeply. Wipe nozzle clean after use and snap cap back onto the bottle.

Other information

- store between 20° to 25°C (68° to 77°F)
- retain carton for future reference on full labeling

Inactive Ingredients

benzalkonium chloride, edetate disodium, polyethylene glycol 400, povidone, propylene glycol, sodium phosphate dibasic, sodium phosphate monobasi dihydrate, water

Questions or comments?

Call toll free 1-800-FOR-AVON

www.avon.com

Principal Display Panel

HeXasheild

ORIGINAL

NASAL RELIEF SPRAY

CONGESTION RELIEF

Oxymetazoline HCl-

Nasal Decongestant

Compare to the active ingredient in Afrin®Original

Rapid & Powerful Congestion

Relief 12 Hour Relief

AVON

- Original Nasal Spray - 12 HOURS
- Pump Mist
- Anti-Drip

NET WT 0.5 FL oz (15 mL)